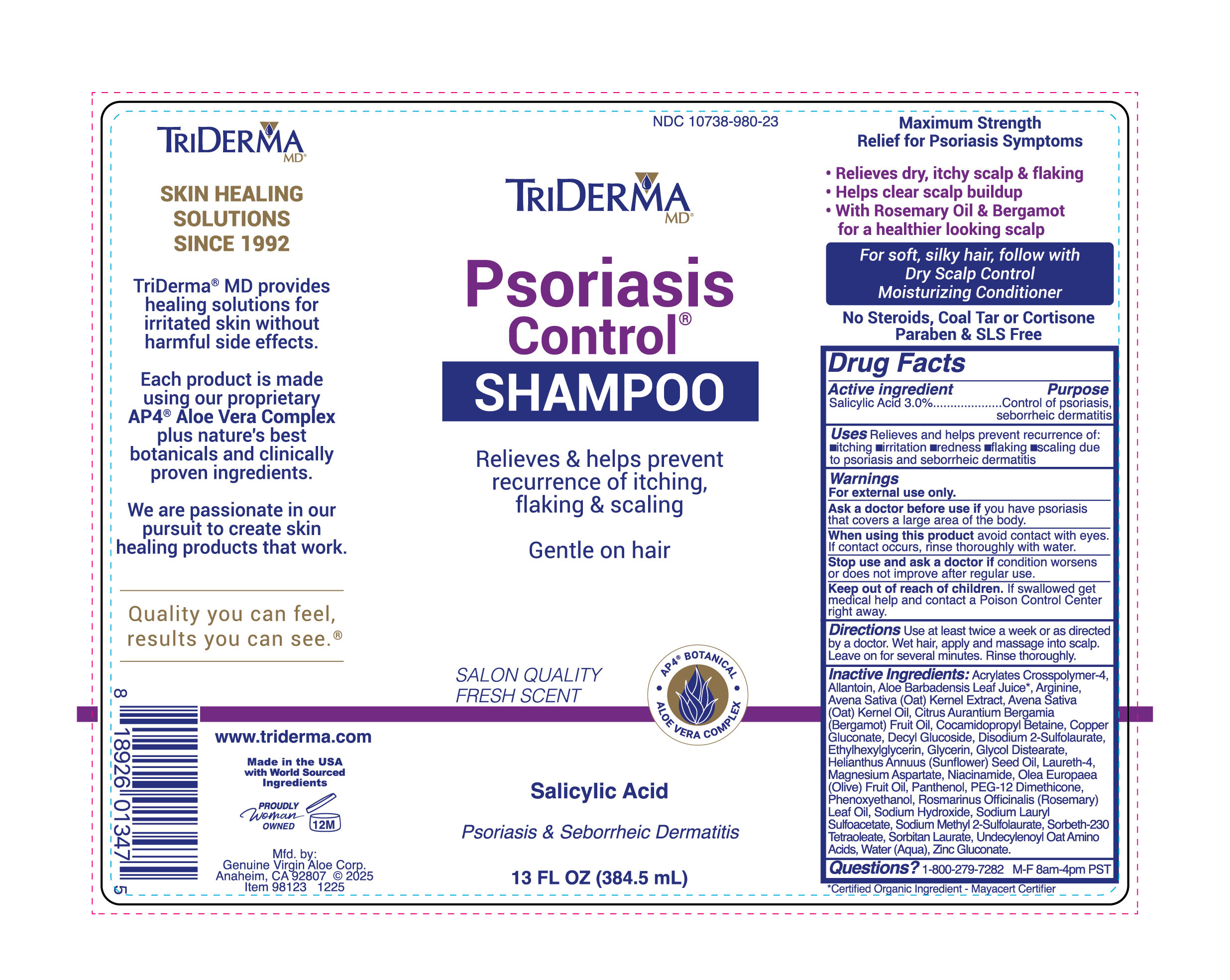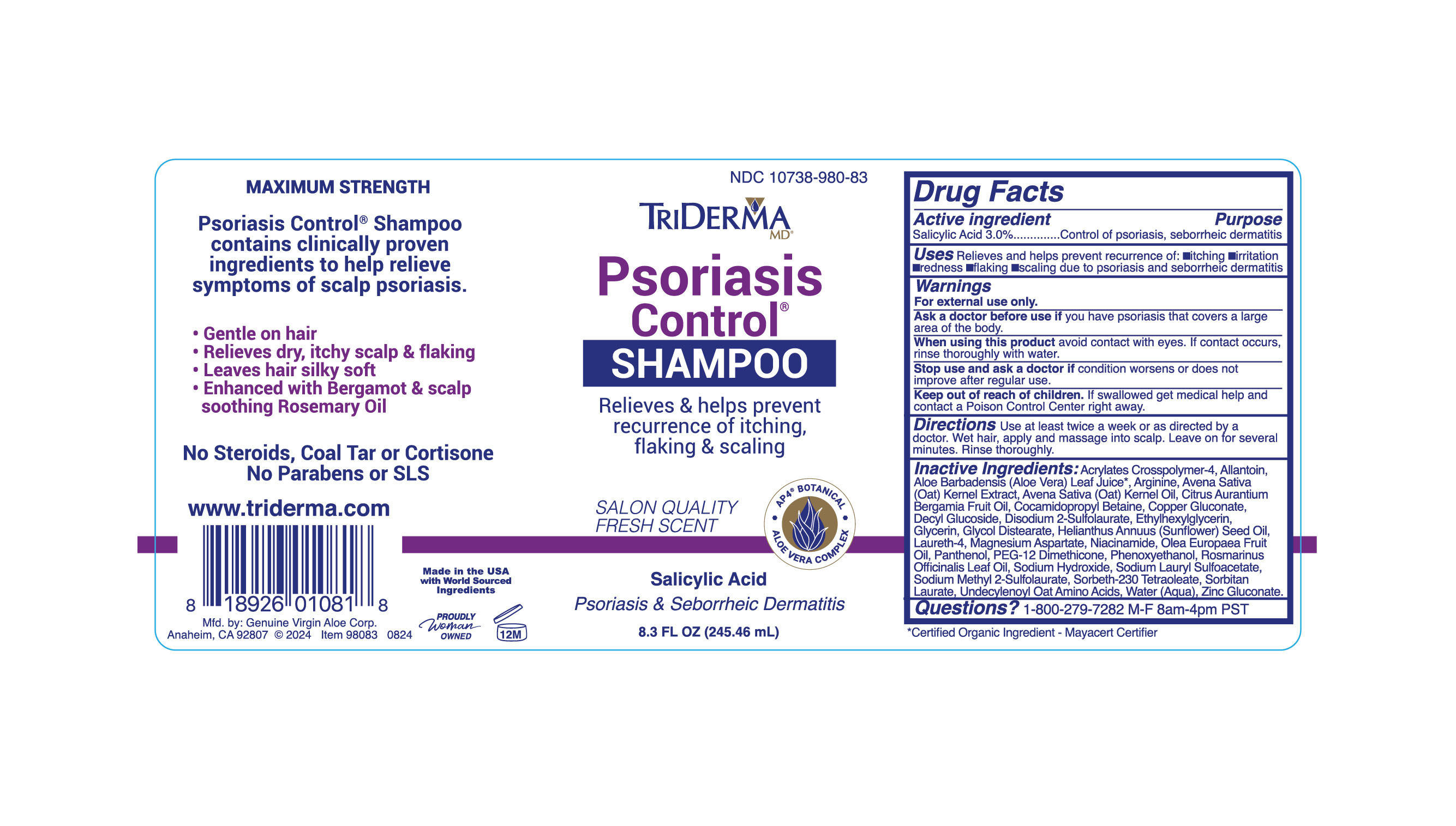 DRUG LABEL: TRIDERMA Psoriasis Control
NDC: 10738-980 | Form: SHAMPOO
Manufacturer: Genuine Virgin Aloe Corporation
Category: otc | Type: HUMAN OTC DRUG LABEL
Date: 20260127

ACTIVE INGREDIENTS: SALICYLIC ACID 3 g/100 mL
INACTIVE INGREDIENTS: ARGININE; OAT AMINO ACIDS; AVENA SATIVA LEAF; SORBETH-30 TETRAOLEATE; SORBITAN LAURATE; NIACINAMIDE; SODIUM LAURYL SULFOACETATE; ACRYLATES CROSSPOLYMER-6; BERGAMOT OIL; LAURETH-4; WATER; COCAMIDOPROPYL BETAINE; GLYCOL DISTEARATE; AVENA SATIVA (OAT) KERNEL OIL; ALOE VERA LEAF; SUNFLOWER OIL; GLYCERIN; PANTHENOL; ALLANTOIN; PEG-12 DIMETHICONE; PHENOXYETHANOL; ETHYLHEXYLGLYCERIN; SODIUM HYDROXIDE; SODIUM METHYL 2-SULFOLAURATE; DECYL GLUCOSIDE; DISODIUM 2-SULFOLAURATE; COPPER GLUCONATE; MAGNESIUM ASPARTATE; OLEA EUROPAEA (OLIVE) FRUIT OIL; ZINC GLUCONATE

TRIDERMA Psoriasis Control SHAMPOO

Active ingredient

Salicylic Acid 3.0%

Purpose

Control of Psoriasis, Dermatitis

INDICATIONS AND USAGE

Uses Relieves and helps prevent recurrence of: •itching •irritation •redness •flaking •scaling due to psoriasis and seborrheic dermatitis

WARNINGS

Warnings For external use only. Ask a doctor before use if you have •psoriasis that covers a large area of the body. When using this product •avoid contact with eyes. If contact occurs, rinse thoroughly with water. Stop use and ask a doctor if •condition worsens or does not improve after regular use.

Keep out of reach of children. If swallowed get medical help or contact a Poison Control Center right away.

DOSAGE AND ADMINISTRATION

Directions Use at least twice a week or as directed by a doctor. Wet hair, apply and massage into scalp. Leave on for several minutes. Rinse thoroughly.

Inactive ingredients:

Acrylates Crosspolymer-4, Allantoin, Aloe Barbadensis Leaf Juice•, Arginine, Avena Saliva (Oat) Kernel Extract, Avena Sativa
(Oat) Kernel Oil, Citrus Aurantium Bergamia (Bergamot) Fruit Oil, Cocamidopropyl Betaine, Copper Gluconate, Decyl Gluooside, Disodium 2-Sulfolaurate, Ethylhexylglycerin, Glycerin, Glycol Distearate, Helianthus Annuus (Sunflower) Seed Oil, Laureth-4, Magnesium Aspartate, Niacinamide, Olea Europaea (Olive) Fruit Oil, Panthenol, PEG-12 Dimethioone, Phenoxyethanol, Rosmarinus Officinalis (Rosemary) Leaf Oil, Sodium Hydroxide, Sodium Lauryl Sulfoacetate, Sodium Methyl 2-Sulfolaurate, Sorbeth-230 Tetraoleate, Sorbitan Laurate, Uncecylenoyl Oat Amino Acids, Water (Aqua), Zinc Gluconate.

*Certified Organic Ingredient - Mayacert Certifier

QUESTIONS

Questions? 1-800-279-7282 M-F 8am-4pm PST

Relieves & helps prevent recurrence of itching, flaking & scaling

• AP4® BOTANICAL • ALOE VERA COMPLEX

Psoriasis & Seborrheic Dermatitis

EXPERTS IN SKIN HEALING SINCE 1992

Psoriasis Control® Shampoo contains clinically proven ingredients that help soothe and relieve psoriasis symptoms.

• Gentle on hair
• Relieves dry, itchy scalp & flaking
• Leaves hair silky soft

No Steroids, Coal Tar or Cortisone Paraben & SLS Free

• Soothes dry, itchy scalp

• Relieves redness & flaking

QUALITY YOU CAN FEEL

RESULTS YOU CAN SEE.®

TriDerma MD® provides healing solutions for irritated skin without harmful side effects.

www.triderma.com

Mfd. by: Genuine Virgin Aloe Corp.,
Anaheim, CA 92807